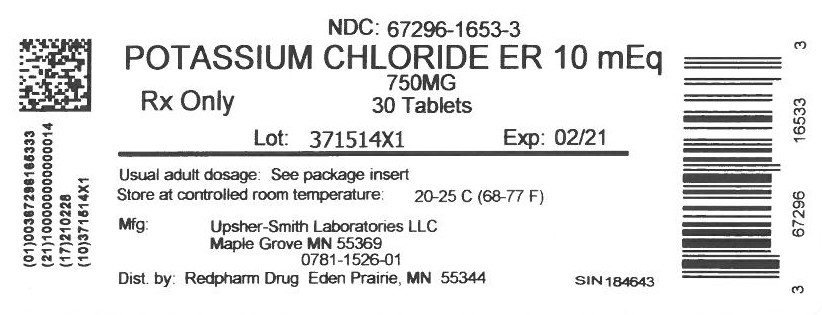 DRUG LABEL: Potassium Chloride
NDC: 67296-1653 | Form: TABLET, FILM COATED, EXTENDED RELEASE
Manufacturer: RedPharm Drug, Inc.
Category: prescription | Type: HUMAN PRESCRIPTION DRUG LABEL
Date: 20210114

ACTIVE INGREDIENTS: POTASSIUM CHLORIDE 750 mg/1 1
INACTIVE INGREDIENTS: HYDROGENATED COTTONSEED OIL; MAGNESIUM STEARATE; POLYETHYLENE GLYCOL, UNSPECIFIED; POLYVINYL ALCOHOL, UNSPECIFIED; SILICON DIOXIDE; TALC; TITANIUM DIOXIDE

Potassium Chloride Extended-Release 750MG

Rx Only

DESCRIPTION

Potassium chloride extended-release tablets, USP are a solid oral dosage form of potassium chloride. Each contains 600 mg or 750 mg of potassium chloride equivalent to 8 mEq or 10 mEq of potassium in a wax matrix tablet. This formulation is intended to provide an extended-release of potassium from the matrix to minimize the likelihood of producing high, localized concentrations of potassium within the gastrointestinal tract.

Potassium chloride extended-release tablets, USP are an electrolyte replenisher. The chemical name is potassium chloride, and the structural formula is KCI. Potassium chloride, USP is a white, granular powder or colorless crystals. It is odorless and has a saline taste. Its solutions are neutral to litmus. It is freely soluble in water and insoluble in alcohol.

Inactive Ingredients

Hydrogenated vegetable oil, magnesium stearate, polyethylene glycol, polyvinyl alcohol, silicon dioxide, talc and titanium dioxide. Dark blue tablets also contain FD&C Blue No. 1 aluminum lake.

CLINICAL PHARMACOLOGY

The potassium ion is the principal intracellular cation of most body tissues. Potassium ions participate in a number of essential physiological processes including the maintenance of intracellular tonicity, the transmission of nerve impulses, the contraction of cardiac, skeletal and smooth muscle and the maintenance of normal renal function.

The intracellular concentration of potassium is approximately 150 to 160 mEq per liter. The normal adult plasma concentration is 3.5 to 5 mEq per liter. An active ion transport system maintains this gradient across the plasma membrane.

Potassium is a normal dietary constituent and under steady-state conditions the amount of potassium absorbed from the gastrointestinal tract is equal to the amount excreted in the urine. The usual dietary intake of potassium is 50 to 100 mEq per day.

Potassium depletion will occur whenever the rate of potassium loss through renal excretion and/or loss from the gastrointestinal tract exceeds the rate of potassium intake. Such depletion usually develops slowly as a consequence of prolonged therapy with oral diuretics, primary or secondary hyperaldosteronism, diabetic ketoacidosis, severe diarrhea, or inadequate replacement of potassium in patients on prolonged parenteral nutrition. Depletion can develop rapidly with severe diarrhea, especially if associated with vomiting. Potassium depletion due to these causes is usually accompanied by a concomitant loss of chloride and is manifested by hypokalemia and metabolic alkalosis. Potassium depletion may produce weakness, fatigue, disturbances of cardiac rhythm (primarily ectopic beats), prominent U-waves in the electrocardiogram and, in advanced cases, flaccid paralysis and/or impaired ability to concentrate urine.

If potassium depletion associated with metabolic alkalosis cannot be managed by correcting the fundamental cause of the deficiency, e.g., where the patient requires long-term diuretic therapy, supplemental potassium in the form of high potassium food or potassium chloride may be able to restore normal potassium levels.

In rare circumstances (e.g., patients with renal tubular acidosis) potassium depletion may be associated with metabolic acidosis and hyperchloremia. In such patients potassium replacement should be accomplished with potassium salts other than the chloride, such as potassium bicarbonate, potassium citrate, potassium acetate or potassium gluconate.

The potassium chloride in potassium chloride extended-release is completely absorbed before it leaves the small intestine. The wax matrix is not absorbed and is excreted in the feces; in some instances the empty matrices may be noticeable in the stool. When the bioavailability of the potassium ion from the potassium chloride extended-release is compared to that of a true solution the extent of absorption is similar.

The extended-release properties of potassium chloride extended-release tablets are demonstrated by the finding that a significant increase in time is required for renal excretion of the first 50% of the potassium chloride extended-release tablets dose as compared to the solution.

Increased urinary potassium excretion is first observed 1 hour after administration of potassium chloride extended-release tablets, reaches a peak at approximately 4 hours, and extends up to 8 hours. Mean daily steady-state plasma levels of potassium following daily administration of potassium chloride extended-release tablets cannot be distinguished from those following administration of potassium chloride solution or from control plasma levels of potassium ion.

INDICATIONS AND USAGE

BECAUSE OF REPORTS OF INTESTINAL AND GASTRIC ULCERATION AND BLEEDING WITH EXTENDED-RELEASE POTASSIUM CHLORIDE PREPARATIONS, THESE DRUGS SHOULD BE RESERVED FOR THOSE PATIENTS WHO CANNOT TOLERATE OR REFUSE TO TAKE LIQUID OR EFFERVESCENT POTASSIUM PREPARATIONS OR FOR PATIENTS IN WHOM THERE IS A PROBLEM OF COMPLIANCE WITH THESE PREPARATIONS.

1. For the therapeutic use of patients with hypokalemia, with or without metabolic alkalosis; in digitalis intoxication; and in patients with hypokalemic familial periodic paralysis. If hypokalemia is the result of diuretic therapy, consideration should be given to the use of a lower dose of diuretic, which may be sufficient without leading to hypokalemia.
2. For the prevention of hypokalemia in patients who would be at particular risk if hypokalemia were to develop, e.g., digitalized patients or patients with significant cardiac arrhythmias.

The use of potassium salts in patients receiving diuretics for uncomplicated essential hypertension is often unnecessary when such patients have a normal dietary pattern and when low doses of the diuretic are used. Serum potassium should be checked periodically, however, and if hypokalemia occurs, dietary supplementation with potassium-containing foods may be adequate to control milder cases. In more severe cases, and if dose adjustment of the diuretic is ineffective or unwarranted, supplementation with potassium salts may be indicated.

CONTRAINDICATIONS

Potassium supplements are contraindicated in patients with hyperkalemia since a further increase in serum potassium concentration in such patients can produce cardiac arrest. Hyperkalemia may complicate any of the following conditions: chronic renal failure, systemic acidosis such as diabetic acidosis, acute dehydration, extensive tissue breakdown as in severe burns, adrenal insufficiency or the administration of a potassium-sparing diuretic (e.g., spironolactone, triamterene or amiloride) [see OVERDOSAGE].

Extended-release formulations of potassium chloride have produced esophageal ulceration in certain cardiac patients with esophageal compression due to an enlarged left atrium. Potassium supplementation, when indicated in such patients, should be given as a liquid preparation.

All solid oral dosage forms of potassium chloride are contraindicated in any patient in whom there is structural, pathological (e.g., diabetic gastroparesis) or pharmacologic (use of anticholinergic agents or other agents with anticholinergic properties at sufficient doses to exert anticholinergic effects) cause for arrest or delay in tablet passage through the gastrointestinal tract.

WARNINGS

Hyperkalemia

[see OVERDOSAGE]

In patients with impaired mechanisms for excreting potassium, the administration of potassium salts can produce hyperkalemia and cardiac arrest. This occurs most commonly in patients given potassium by the intravenous route but may also occur in patients given potassium orally. Potentially fatal hyperkalemia can develop rapidly and be asymptomatic.

The use of potassium salts in patients with chronic renal disease, or any other condition which impairs potassium excretion, requires particularly careful monitoring of the serum potassium concentration and appropriate dosage adjustment.

Interaction with Potassium-sparing Diuretics

Hypokalemia should not be treated by the concomitant administration of potassium salts and a potassium-sparing diuretic (e.g., spironolactone, triamterene or amiloride), since the simultaneous administration of these agents can produce severe hyperkalemia.

Interaction with Angiotensin-Converting Enzyme Inhibitors

Angiotensin-converting enzyme (ACE) inhibitors (e.g., captopril, enalapril) will produce some potassium retention by inhibiting aldosterone production. Potassium supplements should be given to patients receiving ACE inhibitors only with close monitoring.

Gastrointestinal Lesions

Solid oral dosage forms of potassium chloride can produce ulcerative and/or stenotic lesions of the gastrointestinal tract. Based on spontaneous adverse reaction reports, enteric-coated preparations of potassium chloride are associated with an increased frequency of small bowel lesions (40 to 50 per 100,000 patient years) compared to extended-release wax matrix formulations (less than one per 100,000 patient years). Because of the lack of extensive marketing experience with microencapsulated products, a comparison between such products and wax matrix or enteric-coated products is not available. Potassium chloride extended-release tablets are wax matrix tablets formulated to provide an extended rate of release of potassium chloride and thus to minimize the possibility of high local concentration of potassium near the gastrointestinal wall.

Prospective trials have been conducted in normal human volunteers in which the upper gastrointestinal tract was evaluated by endoscopic inspection before and after one week of solid oral potassium chloride therapy. The ability of this model to predict events occurring in usual clinical practice is unknown. Trials which approximated usual clinical practice did not reveal any clear differences between the wax matrix and microencapsulated dosage forms. In contrast, there was a higher incidence of gastric and duodenal lesions in subjects receiving a high dose of a wax matrix extended-release formulation under conditions which did not resemble usual or recommended clinical practice (i.e., 96 mEq per day in divided doses of potassium chloride administered to fasted patients, in the presence of an anticholinergic drug to delay gastric emptying). The upper gastrointestinal lesions observed by endoscopy were asymptomatic and were not accompanied by evidence of bleeding (hemoccult testing). The relevance of these findings to the usual conditions (i.e., non-fasting, no anticholinergic agent, smaller doses) under which extended-release potassium chloride products are used is uncertain; epidemiologic studies have not identified an elevated risk, compared to microencapsulated products, for upper gastrointestinal lesions in patients receiving wax matrix formulations. Potassium chloride extended-release tablets should be discontinued immediately and the possibility of ulceration, obstruction or perforation considered if severe vomiting, abdominal pain, distention or gastrointestinal bleeding occurs.

Metabolic Acidosis

Hypokalemia in patients with metabolic acidosis should be treated with an alkalinizing potassium salt such as potassium bicarbonate, potassium citrate, potassium acetate or potassium gluconate.

PRECAUTIONS

General

The diagnosis of potassium depletion is ordinarily made by demonstrating hypokalemia in a patient with a clinical history suggesting some cause for potassium depletion. In interpreting the serum potassium level, the physician should be aware that acute alkalosis per se can produce hypokalemia in the absence of a deficit in total body potassium while acute acidosis per se can increase the serum potassium concentration into the normal range even in the presence of a reduced total body potassium. The treatment of potassium depletion, particularly in the presence of cardiac disease, renal disease or acidosis requires careful attention to acid-base balance and appropriate monitoring of serum electrolytes, the electrocardiogram and the clinical status of the patient.

Information for Patients

Physicians should consider reminding the patient of the following:

- To take each dose with meals and with a full glass of water or other liquid.
- To take this medicine following the frequency and amount prescribed by the physician. This is especially important if the patient is also taking diuretics and/or digitalis preparations.
- To check with the physician if there is trouble swallowing the tablets or if the tablets seem to stick in the throat.
- To check with the physician at once if tarry stools or other evidence of gastrointestinal bleeding is noticed.
- To take each dose without crushing, chewing or sucking the tablets.

Laboratory Tests

When blood is drawn for analysis of plasma potassium it is important to recognize that artifactual elevations can occur after improper venipuncture technique or as a result of in vitro hemolysis of the sample.

Drug Interactions

Potassium-sparing diuretic, angiotensin-converting enzyme inhibitors [see WARNINGS].

Carcinogenesis, Mutagenesis, Impairment of Fertility

Carcinogenicity, mutagenicity and fertility studies in animals have not been performed. Potassium is a normal dietary constituent.

Pregnancy

Pregnancy Category C

Animal reproduction studies have not been conducted with potassium chloride extended-release tablets. It is unlikely that potassium supplementation that does not lead to hyperkalemia would have an adverse effect on the fetus or would affect reproductive capacity.

Nursing Mothers

The normal potassium ion content of human milk is about 13 mEq per liter. It is not known if potassium chloride extended-release tablets have an effect on this content. Since oral potassium becomes part of the body potassium pool, so long as body potassium is not excessive, the contribution of potassium chloride supplementation should have little or no effect on the level in human milk.

Pediatric Use

Safety and effectiveness in the pediatric population have not been established.

Geriatric Use

Clinical studies of potassium chloride extended-release did not include sufficient numbers of subjects aged 65 and over to determine whether they respond differently from younger subjects. Other reported clinical experience has not identified differences in responses between the elderly and younger patients. In general, dose selection for an elderly patient should be cautious, usually starting at the low end of the dosing range, reflecting the greater frequency of decreased hepatic, renal or cardiac function, and of concomitant disease or other drug therapy.

This drug is known to be substantially excreted by the kidney, and the risk of toxic reactions to this drug may be greater in patients with impaired renal function. Because elderly patients are more likely to have decreased renal function, care should be taken in dose selection, and it may be useful to monitor renal function.

ADVERSE REACTIONS

One of the most severe adverse effects is hyperkalemia [see CONTRAINDICATIONS, WARNINGS and OVERDOSAGE]. There also have been reports of upper and lower gastrointestinal conditions including obstruction, bleeding, ulceration and perforation [see CONTRAINDICATIONS and WARNINGS].

The most common adverse reactions to oral potassium salts are nausea, vomiting, flatulence, abdominal pain/discomfort and diarrhea. These symptoms are due to irritation of the gastrointestinal tract and are best managed by taking the dose with meals or reducing the amount taken at one time.

Skin rash has been reported rarely.

OVERDOSAGE

The administration of oral potassium salts to persons with normal excretory mechanisms for potassium rarely causes serious hyperkalemia. However, if excretory mechanisms are impaired, or if potassium is administered too rapidly intravenously, potentially fatal hyperkalemia can result [see CONTRAINDICATIONS and WARNINGS]. It is important to recognize that hyperkalemia is usually asymptomatic and may be manifested only by an increased serum potassium concentration (6.5 to 8.0 mEq/L) and characteristic electrocardiographic changes (peaking of T-waves, loss of P-waves, depression of S-T segment and prolongation of the QT interval). Late manifestations include muscle paralysis and cardiovascular collapse from cardiac arrest (9 to 12 mEq/L).

Treatment measures for hyperkalemia include the following:

1. Elimination of foods and medications containing potassium and of any agents with potassium-sparing properties.
2. Intravenous administration of 300 to 500 mL/hr of 10% dextrose solution containing 10 to 20 units of crystalline insulin per 1,000 mL.
3. Correction of acidosis, if present, with intravenous sodium bicarbonate.
4. Use of exchange resins, hemodialysis or peritoneal dialysis.

In treating hyperkalemia, it should be recalled that in patients who have been stabilized on digitalis, too rapid a lowering of the serum potassium concentration can produce digitalis toxicity.

The extended-release feature means that absorption and toxic effects may be delayed for hours. Consider standard measures to remove any unabsorbed drug.

DOSAGE AND ADMINISTRATION

The usual dietary potassium intake by the average adult is 50 to 100 mEq per day. Potassium depletion sufficient to cause hypokalemia usually requires the loss of 200 mEq or more of potassium from the total body store.

Dosage must be adjusted to the individual needs of each patient. The dose for the prevention of hypokalemia is typically in the range of 20 mEq per day. Doses of 40 to 100 mEq per day or more are used for the treatment of potassium depletion. Dosage should be divided if more than 20 mEq per day is given such that no more than 20 mEq is given in a single dose.

Each potassium chloride extended-release tablet provides 8 mEq or 10 mEq of potassium chloride.

Potassium chloride extended-release tablets should be taken with meals and with a glass of water or other liquid. This product should not be taken on an empty stomach because of its potential for gastric irritation [see WARNINGS].

NOTE: Potassium chloride extended-release tablets must be swallowed whole and never crushed, chewed or sucked.

HOW SUPPLIED

Potassium chloride extended-release tablets, USP, 600 mg potassium chloride (equivalent to 8 mEq) are dark-blue, round, film-coated tablets and debossed with "USL 8". They are supplied as follows.

 | Bottles of 100 tablets | NDC 0781-1516-01
 | Bottles of 1,000 tablets | NDC 0781-1516-10

Potassium chloride extended-release tablets, USP, 750 mg potassium chloride (equivalent to 10 mEq) are white, round, film coated tablets and debossed with "USL 10". They are supplied as follows.

 | Bottles of 100 tablets | NDC 0781-1526-01
 | Bottles of 1,000 tablets | NDC 0781-1526-10

STORAGE AND HANDLING

Store at 20° to 25°C (68° to 77°F); excursions permitted to 15° to 30°C (59° to 86°F) [see USP Controlled Room Temperature].

Protect from light and moisture.

Dispense in a tight container with a child-resistant closure.

Manufactured by
Upsher-Smith Laboratories, LLC
Maple Grove, MN 55369
for
Sandoz Inc.
Princeton, NJ 08540

Revised October, 2017